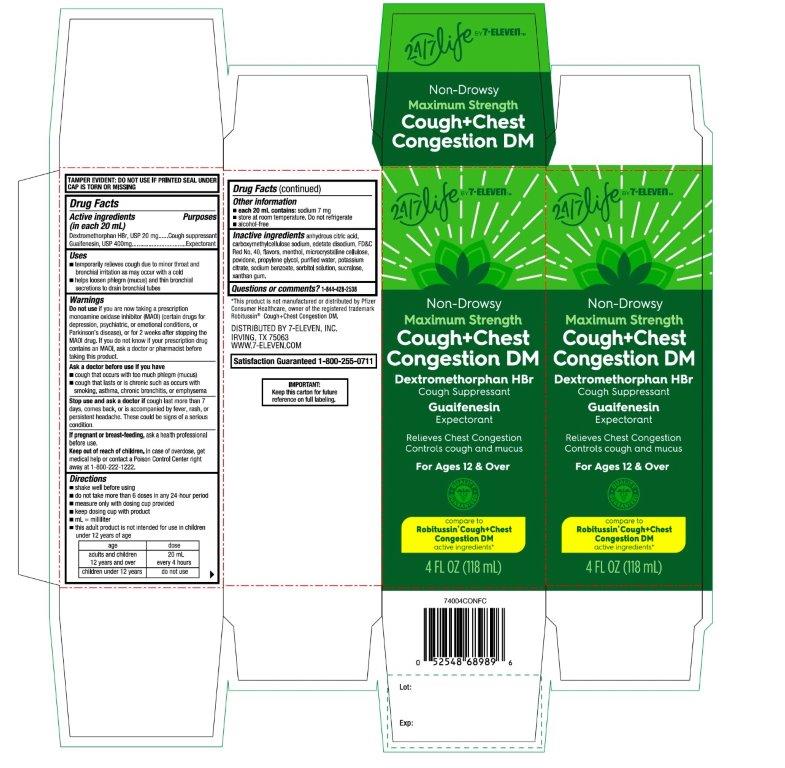 DRUG LABEL: 7 Select

NDC: 10202-740 | Form: SOLUTION
Manufacturer: 7-ELEVEN
Category: otc | Type: HUMAN OTC DRUG LABEL
Date: 20250718

ACTIVE INGREDIENTS: DEXTROMETHORPHAN HYDROBROMIDE 20 mg/20 mL; GUAIFENESIN 400 mg/20 mL
INACTIVE INGREDIENTS: ANHYDROUS CITRIC ACID; CARBOXYMETHYLCELLULOSE SODIUM, UNSPECIFIED; EDETATE DISODIUM; FD&C RED NO. 40; MENTHOL, UNSPECIFIED FORM; MICROCRYSTALLINE CELLULOSE; POVIDONE, UNSPECIFIED; PROPYLENE GLYCOL; WATER; POTASSIUM CITRATE; SODIUM BENZOATE; SORBITOL; SUCRALOSE; XANTHAN GUM

7-ELEVEN Non-Drowsy Maximum Strength Drug Facts

Active ingredients (in each 20 mL)

Dextromethorphan HBr, USP 20 mg

Guaifenesin, USP 400 mg

Purposes

Cough suppressant

Expectorant

Uses

- temporarily relieves cough due to minor throat and bronchial irritation as may occur with a cold
- helps loosen phlegm (mucus) and thin bronchial secretions to drain bronchial tubes

Do not use

if you are now taking a prescription monoamine oxidase inhibitor (MAOI) (certain drugs for depression, psychiatric, or emotional conditions, or Parkinson’s disease), or for 2 weeks after stopping the MAOI drug. If you do not know if your prescription drug contains an MAOI, ask a doctor or pharmacist before taking this product.

Ask a doctor before use if you have

- cough that occurs with too much phlegm (mucus)
- cough that lasts or is chronic such as occurs with smoking, asthma, chronic bronchitis, or emphysema

Stop use and ask a doctor if

cough lasts for more than 7 days, comes back, or is accompanied by fever, rash, or persistent headache. A persistent cough may be a sign of a serious condition.

If pregnant or breast-feeding,

ask a health professional before use.

Keep out of reach of children.

In case of overdose, get medical help or contact a Poison Control Center right away at (1-800-222-1222).

Directions

- shake well before using
- do not take more than 6 doses in any 24-hour period
- measure only with dosing cup provided
- keep dosing cup with product
- mL = milliliter
- this adult product is not intended for use in children under 12 years of age

age | dose
adults and children 12 years and over | 20 mL every 4 hours
children under 12 years | do not use

Other information

- each 20 mL contains:sodium 7 mg
- store at room temperature. Do not refrigerate.
- Alcohol-free

Inactive ingredients

anhydrous citric acid, carboxymethylcellulose sodium, edetate disodium, FD&C Red No. 40, flavor, menthol, microcrystalline cellulose, povidone, propylene glycol, purified water, potassium citrate, sodium benzoate, sorbitol solution, sucralose, xanthan gum.

Questions or comments?

1-844-428-2538

Package/Label Principal Display Panel

Compare to Robitussin® Cough + Chest CONGESTION DM the active ingredients*

NDC# 10202-740-04

Non-Drowsy

Maximum Strength

Cough + Chest Congestion DM

Dextromethorphan HBr

Cough Suppressant

Guaifenesin

Expectorant

Relieves Chest Congestion Controls cough and mucus

QUALITY GUARANTEED

For Ages 12 & Over

4 FL OZ (118 mL)

DISTRIBUTED BY 7-ELEVEN, INC.

IRVING, TX 75063

WWW.7-ELEVEN.COM

SATISFACTION GUARANTEED 1-800-255-0711

IMPORTANT:Keep this carton for future reference on full labeling.

*This product is not manufactured or distributed by Pfizer Consumer Healthcare, owner of the registered trademark Robitussin®Cough + Congestion DM.